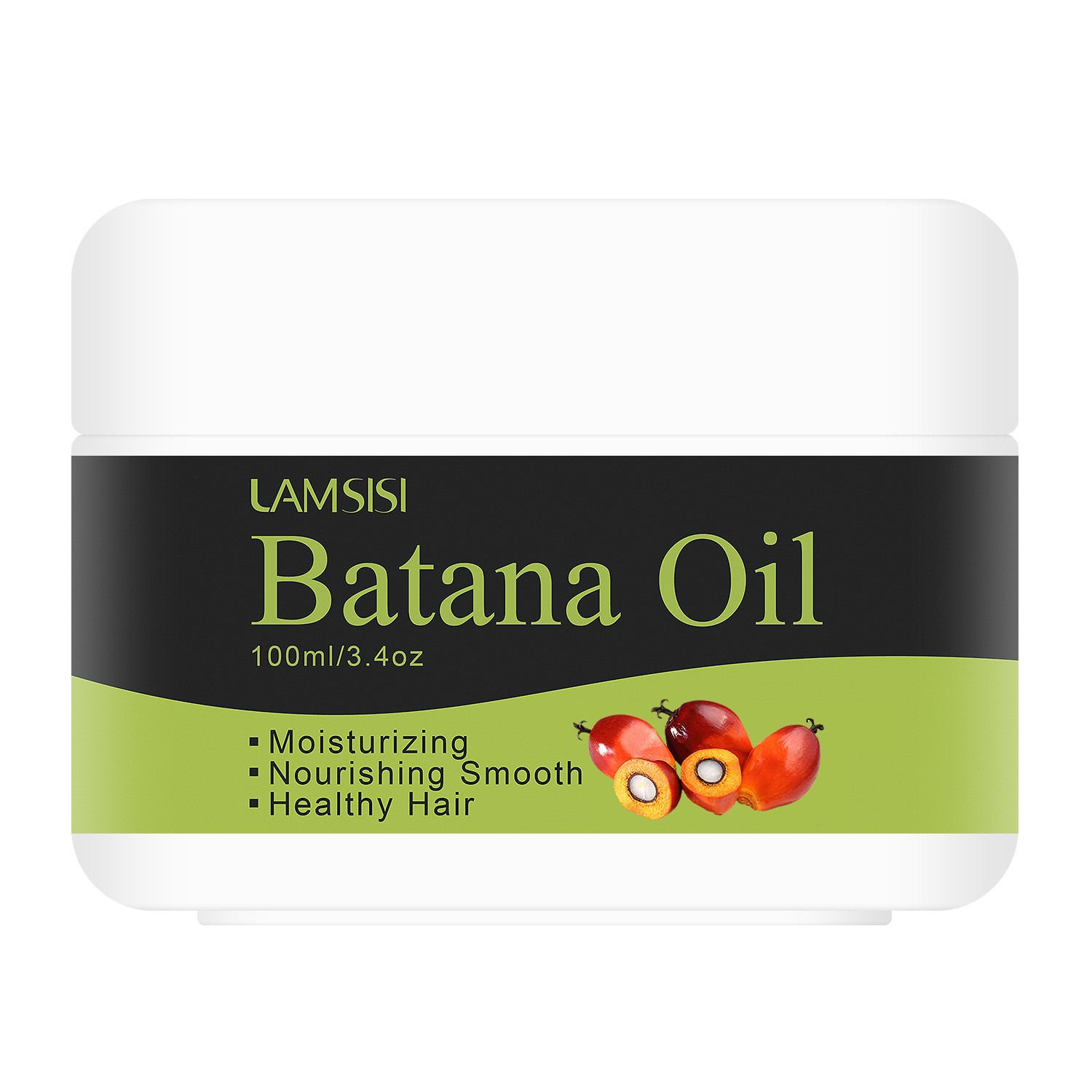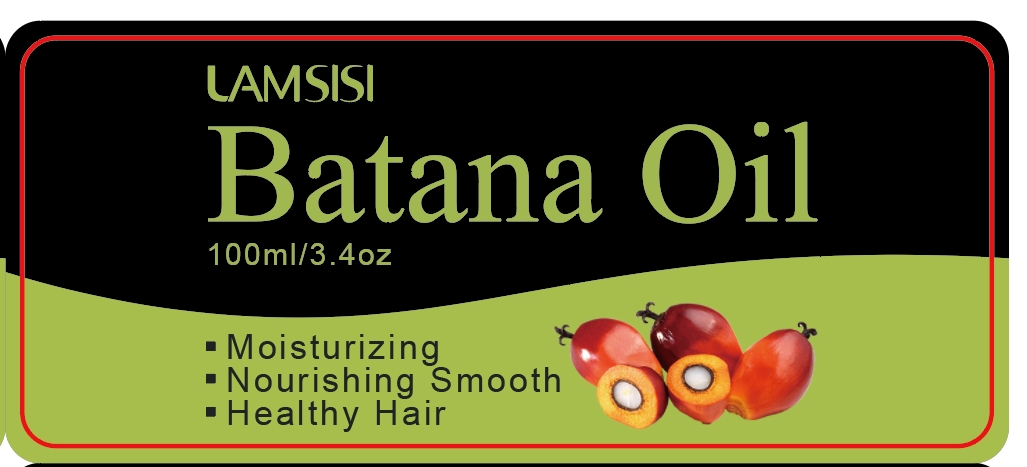 DRUG LABEL: Batana Oil
NDC: 84025-172 | Form: OIL
Manufacturer: Guangzhou Yanxi Biotechnology Co.. Ltd
Category: otc | Type: HUMAN OTC DRUG LABEL
Date: 20240827

ACTIVE INGREDIENTS: SORBITOL 5 mg/100 mL; DIMETHICONE 3 mg/100 mL
INACTIVE INGREDIENTS: WATER

DOSAGE AND ADMINISTRATION

Hair care oil for nourishing scalp and smoothing hair

WARNINGS

keep out of children

INACTIVE INGREDIENT

AQUA

INDICATIONS AND USAGE

For daily scalp and hair care

Keep out of children

PURPOSE

Effectively maintain scalp health and relieve dry hair problems